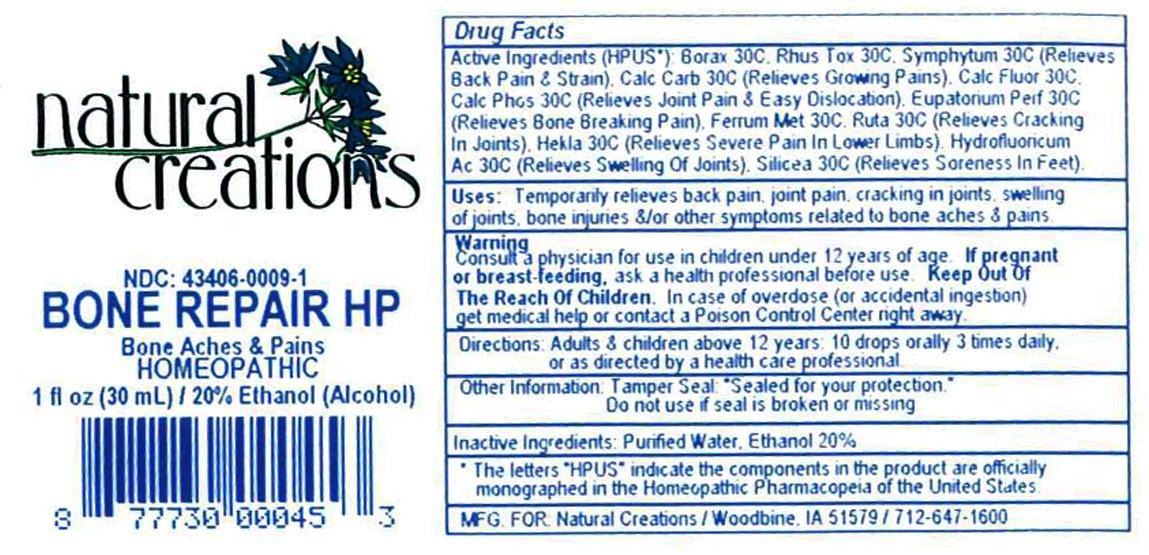 DRUG LABEL: BONE REPAIR HP
NDC: 43406-0009 | Form: LIQUID
Manufacturer: Natural Creations, Inc.
Category: homeopathic | Type: HUMAN OTC DRUG LABEL
Date: 20121003

ACTIVE INGREDIENTS: SODIUM BORATE 30 [hp_C]/1 mL; CALCIUM CARBONATE 30 [hp_C]/1 mL; CALCIUM FLUORIDE 30 [hp_C]/1 mL; TRIBASIC CALCIUM PHOSPHATE 30 [hp_C]/1 mL; EUPATORIUM PERFOLIATUM FLOWERING TOP 30 [hp_C]/1 mL; IRON 30 [hp_C]/1 mL; HEKLA LAVA 30 [hp_C]/1 mL; HYDROFLUORIC ACID 30 [hp_C]/1 mL; TOXICODENDRON PUBESCENS LEAF 30 [hp_C]/1 mL; RUTA GRAVEOLENS FLOWERING TOP 30 [hp_C]/1 mL; SILICON DIOXIDE 30 [hp_C]/1 mL; COMFREY LEAF 30 [hp_C]/1 mL
INACTIVE INGREDIENTS: WATER; ALCOHOL

BONE REPAIR HP

ACTIVE INGREDIENT

Active Ingredients (HPUS*): Borax Veneta 30C, Calcarea Carbonica 30C, Calcarea Fluorica 30C, Calcarea Phosphorica 30C, Eupatorium Perfoliatum 30C, Ferrum Metallicum 30C, Fluoricum Acidum 30C, Hekla Lava 30C, Rhus Toxicodendron 30C, Ruta Graveolens 30C, Silicea 30C, Symphytum Officinale 30C

INDICATIONS AND USAGE

USES: Temporarily relieves back pain, joint pain, cracking in joints, swelling of joints, bone injuries, &/or other symptoms related to bone aches & pains

WARNINGS

Consult a physician for use in children under 12 years of age. IF PREGNANT OR BREAST-FEEDING, ask a health care professional before use. KEEP OUT OF THE REACH OF CHILDREN. In case of overdose (or accidental ingestino) get medical help or contact a Poison Control Center right away.

DOSAGE AND ADMINISTRATION

DIRECTIONS: Adults and children above 12 years: 10 drops orally 3 times daily, or as directed by a health care professional.

OTHER INFORMATION: Tamper Seal: "Sealed for your protection." Do not use if seal is broken or missing.

REFERENCES

*The letters "HPUS" indicate the components in the product are officially monographed in the Homeopathic Pharmacopeia of the United States.

INACTIVE INGREDIENTS: Purified Water, USP Ethanol Alcohol 20%

QUESTIONS AND COMMENTS?

MFG FOR: Natural Creations / Woodbine, IA / 51579 712.647.1600

LOT:

PURPOSE

USES: Temporarily relieves back pain, joint pain, cracking in joints, swelling of joints, bone injuries, &/or other symptoms related to bone aches & pains.

KEEP OUT OF REACH OF CHILDREN

KEEP OUT OF THE REACH OF CHILDREN. In case of overdose (or accidental ingestion) get medical help or contact a Poison Control Center.

INACTIVE INGREDIENTS: Purified Water, Ethanol Alcohol 20%

PACKAGE LABEL

NDC: 43406-0009-1

BONE REPAIR HP

Bone Aches & Pains

HOMEOPATHIC

1 fl oz (30 mL) / 20% Ethanol (Alcohol)

UPC: 877730000453